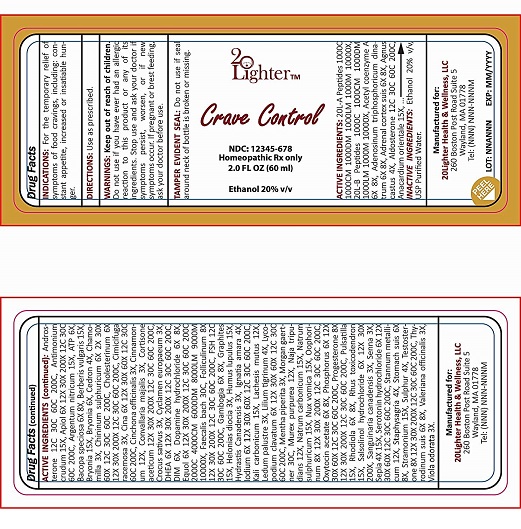 DRUG LABEL: 20Lighter Crave Control
NDC: 70418-001 | Form: LIQUID
Manufacturer: 20Lighter Health & Wellness, LLC
Category: homeopathic | Type: HUMAN PRESCRIPTION DRUG LABEL
Date: 20160520

ACTIVE INGREDIENTS: ESTRONE 8 [hp_X]/60 mL; FOLLITROPIN 12 [hp_C]/60 mL; GAMBOGE 6 [hp_X]/60 mL; CHAMAELIRIUM LUTEUM ROOT 3 [hp_X]/60 mL; HUMULUS LUPULUS POLLEN 15 [hp_X]/60 mL; STRYCHNOS IGNATII SEED 4 [hp_X]/60 mL; IODINE 6 [hp_X]/60 mL; LACHESIS MUTA WHOLE 12 [hp_X]/60 mL; LEDUM PALUSTRE TWIG 3 [hp_X]/60 mL; LILIUM LANCIFOLIUM WHOLE FLOWERING 4 [hp_X]/60 mL; LYCOPODIUM CLAVATUM SPORE 6 [hp_X]/60 mL; MENTHA PIPERITA 3 [hp_X]/60 mL; SULFUR 4 [hp_X]/60 mL; ACETYL COENZYME A 6 [hp_X]/60 mL; .ALPHA.-TOCOPHEROL 6 [hp_X]/60 mL; CHASTE TREE 4 [hp_X]/60 mL; ALDOSTERONE 12 [hp_C]/60 mL; SEMECARPUS ANACARDIUM JUICE 15 [hp_X]/60 mL; ANDROSTERONE 12 [hp_C]/60 mL; SILVER NITRATE 15 [hp_X]/60 mL; ARTEMISIA CINA FLOWER 3 [hp_X]/60 mL; EQUOL, (+)- 6 [hp_X]/60 mL; HYDRASTIS CANADENSIS WHOLE 3 [hp_X]/60 mL; ADENOSINE TRIPHOSPHATE 6 [hp_X]/60 mL; BERBERIS VULGARIS ROOT BARK 15 [hp_X]/60 mL; BRYONIA ALBA ROOT 6 [hp_X]/60 mL; SIMABA CEDRON SEED 4 [hp_X]/60 mL; QUININE SULFATE 6 [hp_X]/60 mL; CHOLESTEROL 6 [hp_X]/60 mL; CINCHONA OFFICINALIS BARK 3 [hp_X]/60 mL; CINNAMOMUM CAMPHORA WHOLE 12 [hp_X]/60 mL; CONVALLARIA MAJALIS 3 [hp_X]/60 mL; CORTISONE ACETATE 12 [hp_X]/60 mL; CROCUS SATIVUS FLOWER 3 [hp_X]/60 mL; CYCLAMEN PURPURASCENS TUBER 3 [hp_X]/60 mL; PRASTERONE 6 [hp_X]/60 mL; MATRICARIA CHAMOMILLA FLOWERING TOP OIL 3 [hp_X]/60 mL; BLACK COHOSH 3 [hp_X]/60 mL; GRAPHITE 15 [hp_X]/60 mL; NAJA NAJA VENOM 12 [hp_X]/60 mL; ALCALIGENES FAECALIS 30 [hp_C]/60 mL; ANTIMONY TRISULFIDE 15 [hp_X]/60 mL; HEXAPLEX TRUNCULUS HYPOBRANCHIAL GLAND JUICE 12 [hp_X]/60 mL; SODIUM SULFATE 15 [hp_X]/60 mL; STRYCHNOS NUX-VOMICA SEED 15 [hp_X]/60 mL; SUS SCROFA OVARY 8 [hp_X]/60 mL; TIN 12 [hp_X]/60 mL; DELPHINIUM STAPHISAGRIA SEED 4 [hp_X]/60 mL; DATURA STRAMONIUM 15 [hp_X]/60 mL; TESTOSTERONE 8 [hp_X]/60 mL; THYROID, UNSPECIFIED 6 [hp_X]/60 mL; VALERIAN 3 [hp_X]/60 mL; VIOLA ODORATA 3 [hp_X]/60 mL; APIOLE (PARSLEY) 6 [hp_X]/60 mL; PHOSPHORUS 6 [hp_X]/60 mL; PROGESTERONE 8 [hp_X]/60 mL; ANEMONE PATENS 15 [hp_X]/60 mL; RHODIOLA KIRILOWII WHOLE 6 [hp_X]/60 mL; TOXICODENDRON PUBESCENS LEAF 15 [hp_X]/60 mL; SANGUINARIA CANADENSIS ROOT 3 [hp_X]/60 mL; SENNA LEAF 3 [hp_X]/60 mL; SEPIA OFFICINALIS JUICE 4 [hp_X]/60 mL
INACTIVE INGREDIENTS: OXYTOCIN ACETATE; SODIUM CARBONATE; 3-O-METHYLDOPAMINE HYDROCHLORIDE; POTASSIUM CARBONATE; SALSOLINOL HYDROCHLORIDE; SEROTONIN HYDROCHLORIDE; ALCOHOL; WATER

PURPOSE

For temporary relief of symptoms of food cravings including: constant appetite, increased or insatiable hunger.

KEEP OUT OF REACH OF CHILDREN

WARNING

Do not use if you have ever had an allergic reaction to this product or any of its ingredients.

Stop use and ask doctor if symptoms persist or worsen, or if new symptoms occurs.

If pregnant or breastfeeding, ask doctor before use.

DOSAGE AND ADMINISTRATION

Use as prescribed

INDICATIONS AND USAGE

Use as prescribed.

ACTIVE INGREDIENTS

20L-A Peptides
20L-B Peptides
Acetyl coenzyme A
adenosinum triphosphoricum dinatrum
adrenal cotex suis
agnus castus
aldosterone
anacardium orientale
androsterone
antimonium crudum
apiol
argentum nitricum
ATP
bacopa speciosa
berberis vulgaris
bryonia
cedron
chamomilla
chininum sulphuricum
cholesterinum
cimicifugaracemosa
cina
cinchona officinalis
cinnamonum
convallaria majalis
cortisone aceticum
crocus sativus
cyclamen europaeum
DHEA
DIM
dopamine hydrochloride
equol
faecalis bach
folliculinum
FSH
gambogia
graphites
helonias diocia
humulus lupulus
hydrastis canadensis
ignatia amara
iodium
kali carbonicum
lachesis mutus
ledum palustre
lilium tigrinum
lycopodium clavatum
mentha piperita
morgan gaertner
murex purpurea
naja tripudians
natrum carbonicum
natrum sulphuricum
nux vomica
oophorinum
oxytocin acetate
phosphorus
progesterone
pulsatilla
rhodiola
rhus toxicodendron
salsolinol hydrochloride
sanguinaria canadensis
senna
sepia
serotonin hydrochloride
stannum metallicum
staphysagria
stomach suis
stramonium
sulphur
testosterone
thyrodinum suis
valeriana officinalis
viola odorata

INACTIVE INGREDIENTS

Ethanol 20%

Purified Water